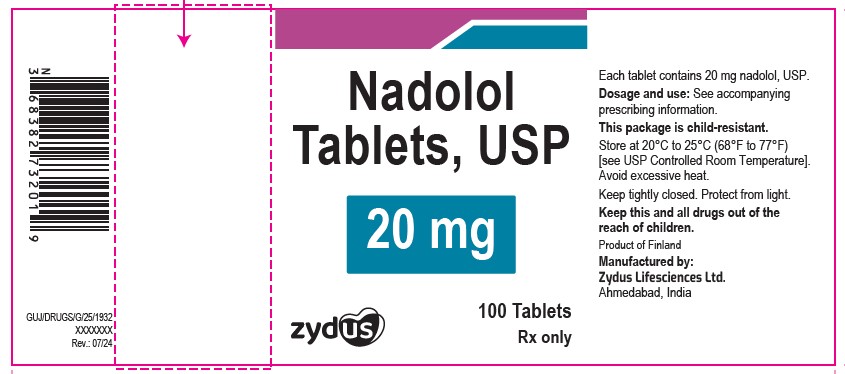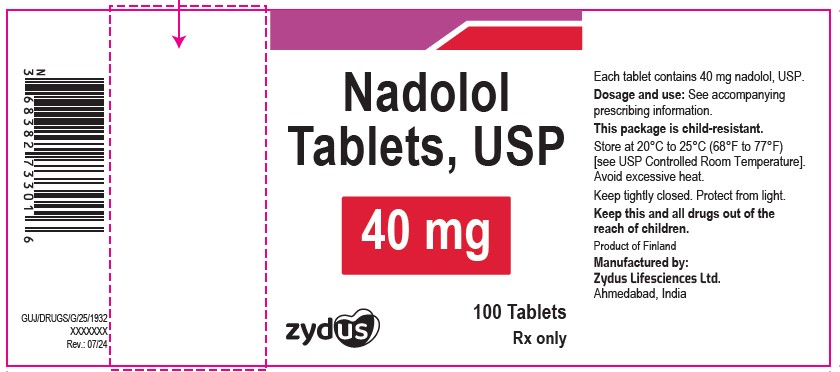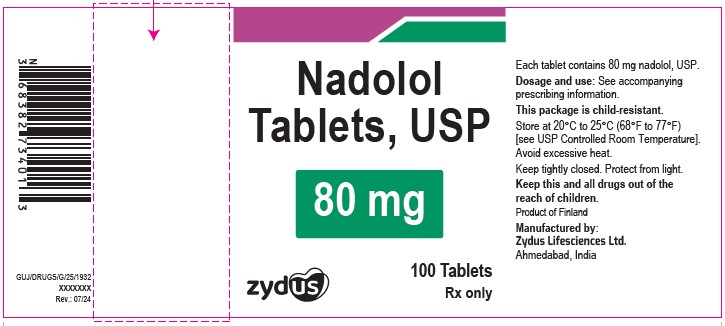 DRUG LABEL: Nadolol
NDC: 70771-1090 | Form: TABLET
Manufacturer: Zydus Lifesciences Limited
Category: prescription | Type: HUMAN PRESCRIPTION DRUG LABEL
Date: 20241205

ACTIVE INGREDIENTS: NADOLOL 40 mg/1 1
INACTIVE INGREDIENTS: ANHYDROUS CITRIC ACID; CELLULOSE, MICROCRYSTALLINE; FERRIC OXIDE YELLOW; MAGNESIUM STEARATE; POVIDONE; SILICON DIOXIDE; SODIUM STARCH GLYCOLATE TYPE A POTATO; STARCH, CORN

Nadolol Tablets, USP

PACKAGE LABEL.PRINCIPAL DISPLAY PANEL

NDC 70771-1089-1

Nadolol tablets, 20 mg

Rx only

100 tablets

NDC 70771-1090-1

Nadolol tablets, 40 mg

Rx only

100 tablets

NDC 70771-1091-1

Nadolol tablets, 80 mg

Rx only

100 tablets